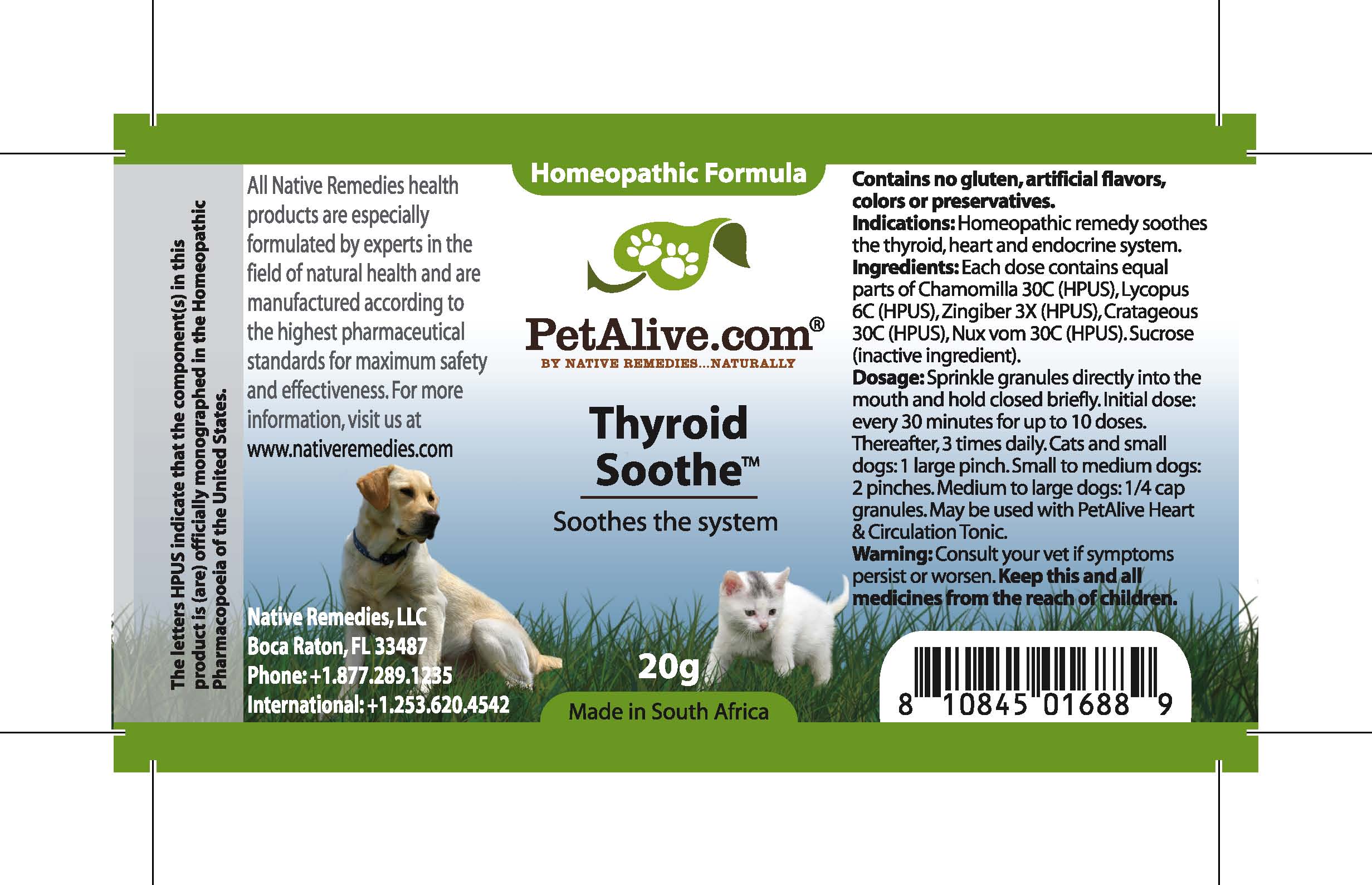 DRUG LABEL: Thyroid Soothe
NDC: 68647-185 | Form: GRANULE
Manufacturer: Feelgood Health
Category: homeopathic | Type: OTC ANIMAL DRUG LABEL
Date: 20100907

ACTIVE INGREDIENTS: MATRICARIA RECUTITA 30 [hp_C]/40 mg; LYCOPUS VIRGINICUS 6 [hp_C]/40 mg; CARDAMOM 3 [hp_X]/40 mg; CRATAEGUS FRUIT 30 [hp_C]/40 mg; STRYCHNOS NUX-VOMICA SEED 30 [hp_C]/40 mg
INACTIVE INGREDIENTS: SUCROSE 20000 mg/20000 mg

THYROID SOOTHE

PURPOSE

Soothes the thyroid, heart and endocrine systems

INDICATIONS AND USAGE

Indications: Homeopathic remedy soothes the thyroid, heart and endocrine system.

DOSAGE AND ADMINISTRATION

Dosage: Sprinkle granules directly into the mouth and hold closed briefly. Initial dose: every 30 minutes for up to 10 doses. Thereafter, 3 times daily. Cats and dogs under 20 lbs: 1 large pinch. Dogs 20-50 lbs: 2 pinches. Dogs over 50 lbs: ¼ cap granules. May be used with Heart and Circulation Tonic™.

GENERAL PRECAUTIONS

Caution: Consult your vet if symptoms persist or worsen. Keep this and all medicines from the reach of children.

ACTIVE INGREDIENT

Ingredients: Each dose contains equal parts of Chamomilla (30C) (HPUS), Lycopus (6C) (HPUS), Zingiber (3X) (HPUS), Cratageous (30C) (HPUS), Nux vom (30C) (HPUS)

Sucrose (inactive ingredient).

WARNINGS

Contains no gluten, artificial flavors, colors or preservatives.

PATIENT COUNSELING INFORMATION

All Native Remedies health products are especially formulated by experts in the field of natural health and are manufactured according to the highest pharmaceutical standards for maximum safety and effectiveness. For more information, visit us at www.petalive.com

Distributed by

Native Remedies, LLC

6531 Park of Commerce Blvd.

Suite 160

Boca Raton, FL 33487

Phone: +1.877.289.1235

International: +1.561.999.8857

The letters HPUS indicate that the component(s) in this product is (are) officially monographed in the Homeopathic Pharmacopoeia of the United States.

KEEP OUT OF REACH OF CHILDREN

Keep this and all medicines from the reach of children.